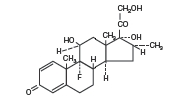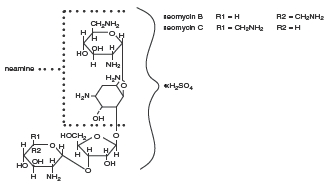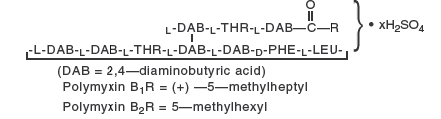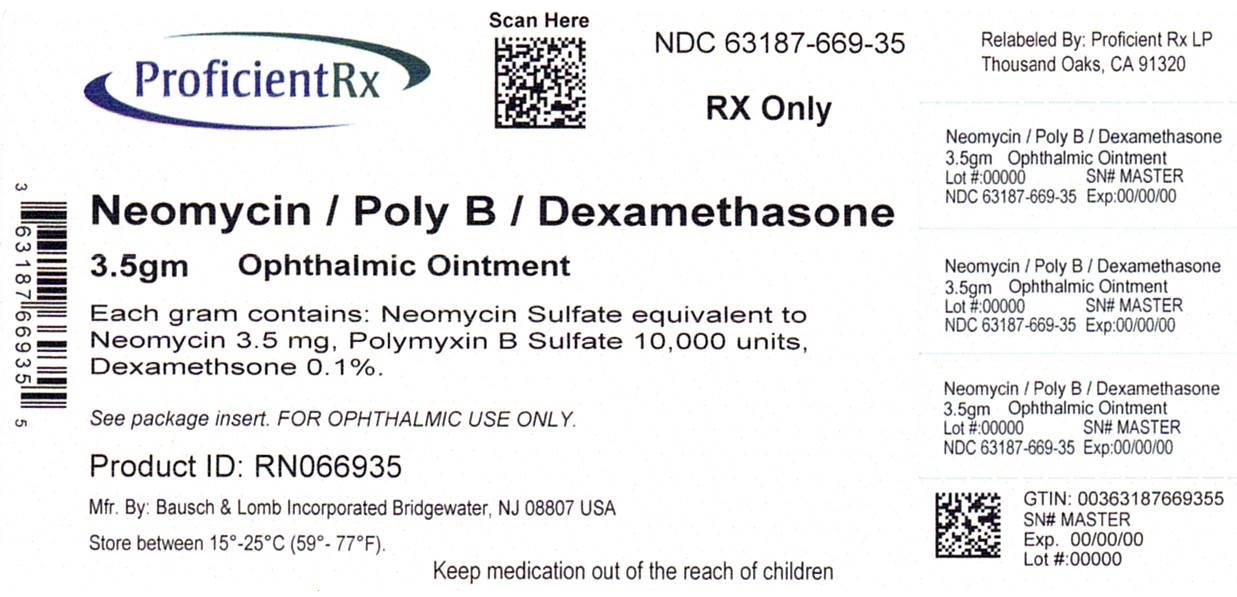 DRUG LABEL: Neomycin and Polymyxin B Sulfates and Dexamethasone
NDC: 63187-669 | Form: OINTMENT
Manufacturer: Proficient Rx LP
Category: prescription | Type: HUMAN PRESCRIPTION DRUG LABEL
Date: 20230501

ACTIVE INGREDIENTS: NEOMYCIN SULFATE 3.5 mg/1 g; POLYMYXIN B SULFATE 10000 [USP'U]/1 g; DEXAMETHASONE 1 mg/1 g
INACTIVE INGREDIENTS: LANOLIN; METHYLPARABEN; MINERAL OIL; PROPYLPARABEN; PETROLATUM

Neomycin and Polymyxin B
Sulfates and Dexamethasone
Ophthalmic Ointment USP

(Sterile)

Rx only

DESCRIPTION:

Neomycin and Polymyxin B Sulfates and Dexamethasone Ophthalmic Ointment USP is a multiple dose anti-infective steroid combination in a sterile ointment for topical application. The active ingredient dexamethasone, is represented by the following structural formula:

C22H29FO5 Mol. Wt. 392.47

Chemical Name: Pregna-1,4-diene-3,20-dione, 9-fluoro-11,17,21-trihydroxy-16-methyl-, (11β,16α)-.

Neomycin Sulfate is the sulfate salt of neomycin B and C which are produced by the growth of Streptomyces fradiae Waksman (Fam. Streptomycetaceae). It has a potency equivalent to not less than 600 micrograms of neomycin base per milligram, calculated on an anhydrous basis. The structural formulae are:

Polymyxin B Sulfate is the sulfate salt of polymyxin B1 and B2 which are produced by the growth of Bacillus polymyxa (Prazmowski) Migula (Fam. Bacillaceae). It has a potency of not less than 6,000 polymyxin B units per milligram, calculated on an anhydrous basis.

The structural formulae are:

Each Gram Contains: ACTIVES: Neomycin Sulfate (equivalent to 3.5 mg Neomycin), Polymyxin B Sulfate, equal to 10,000 polymyxin B units; Dexamethasone 1 mg (0.1%). INACTIVES: White Petrolatum, Lanolin, Mineral Oil.

PRESERVATIVES ADDED: Methylparaben 0.05%, Propylparaben 0.01%.

CLINICAL PHARMACOLOGY:

Corticoids suppress the inflammatory response to a variety of agents and they probably delay or slow the healing. Since corticoids may inhibit the body's defense mechanism against infections, a concomitant antimicrobial drug may be used when this inhibition is considered to be clinically significant in a particular case.

When a decision to administer both a corticoid and an antimicrobial is made, the administration of such drugs in combination has the advantage of greater patient compliance and convenience, with the added assurance that the appropriate dosage of both drugs is administered, plus assured compatibility of ingredients when both types of drugs are in the same formulation and, particularly, that the correct volume of drug is delivered and retained.

The relative potency of corticosteroids depends on the molecular structure, concentration, and release from the vehicle.

INDICATIONS AND USAGE:

For steroid-responsive inflammatory ocular conditions for which a corticosteroid is indicated and where bacterial infection or a risk of bacterial ocular infection exists.

Ocular steroids are indicated in inflammatory conditions of the palpebral and bulbar conjunctiva, cornea, and anterior segment of the globe where the inherent risk of steroid use in certain cases of infective conjunctivitides is accepted to obtain a diminution in edema and inflammation. They are also indicated in chronic anterior uveitis and corneal injury from chemical radiation or thermal burns; or penetration of foreign bodies.

The use of a combination drug with an anti-infective component is indicated where the risk of infection is high or where there is an expectation that potentially dangerous numbers of bacteria will be present in the eye.

The particular anti-infective drugs in this product is active against the following common bacterial eye pathogens: Staphylococcus aureus, Escherichia coli, Haemophilus influenzae, Klebsiella/Enterobacter species, Neisseria species, Pseudomonas aeruginosa.

This product does not provide adequate coverage against Serratia marcescens, and Streptococci, including Streptococcus pneumoniae.

CONTRAINDICATIONS:

Epithelial herpes simplex keratitis (dendritic keratitis), vaccinia, varicella and many other viral diseases of the cornea and conjunctiva. Mycobacterial infection of the eye. Fungal diseases of ocular structures. Hypersensitivity to a component of the medication. (Hypersensitivity to the antibiotic component occurs at a higher rate than for other components.)

WARNINGS:

NOT FOR INJECTION. Do not touch tube tip to any surface, as this may contaminate the contents. Prolonged use may result in glaucoma, with damage to the optic nerve, defects in visual acuity and fields of vision, and posterior subcapsular cataract formation. Prolonged use may suppress the host response and thus increase the hazard of secondary ocular infections. In those diseases causing thinning of the cornea or sclera, perforations have been known to occur with the use of topical steroids. In acute purulent conditions of the eye, steroids may mask infection or enhance existing infection. If these products are used for 10 days or longer, intraocular pressure should be routinely monitored even though it may be difficult in children and uncooperative patients.

Products containing neomycin sulfate may cause cutaneous sensitization.

Employment of steroid medication in the treatment of herpes simplex requires great caution.

PRECAUTIONS:

General

The initial prescription and renewal of the medication order beyond 8 grams should be made by a physician only after examination of the patient with the aid of magnification, such as slit lamp biomicroscopy and, where appropriate, fluorescein staining.

The possibility of persistent fungal infections of the cornea should be considered after prolonged steroid dosing.

Information for Patients:

Do not touch tube tip to any surface, as this may contaminate the contents.

Pregnancy:

Pregnancy Category C. Dexamethasone has been shown to be teratogenic in mice and rabbits following topical ophthalmic application in multiples of the therapeutic dose.

In the mouse, corticosteroids produce fetal resorptions and a specific abnormality, cleft palate. In the rabbit, corticosteroids have produced fetal resorptions and multiple abnormalities involving the head, ears, limbs, palate, etc.

There are no adequate or well-controlled studies in pregnant women. Neomycin, Polymyxin B Sulfates and Dexamethasone Ophthalmic Ointment should be used during pregnancy only if the potential benefit to the mother justifies the potential risk to the embryo or fetus. Infants born of mothers who have received substantial doses of corticosteroids during pregnancy should be observed carefully for signs of hypoadrenalism.

Nursing Mothers:

Systemically administered corticosteroids appear in human milk and could suppress growth, interfere with endogenous corticosteroid production, or cause other untoward effects. It is not known whether topical administration of corticosteroids could result in sufficient systemic absorption to produce detectable quantities in human milk. Because many drugs are excreted in human milk, caution should be exercised when Neomycin, Polymyxin B Sulfates and Dexamethasone Ophthalmic Ointment, is administered to a nursing woman.

Pediatric Use:

Safety and effectiveness in pediatric patients have not been established.

ADVERSE REACTIONS:

Adverse reactions have occurred with steroid/anti-infective combination drugs which can be attributed to the steroid component, the anti-infective component, or the combination. Exact incidence figures are not available since no denominator of treated patients is available.

Reactions occurring most often from the presence of the anti-infective ingredients are allergic sensitizations. The reactions due to the steroid component are: elevation of intraocular pressure (IOP) with possible development of glaucoma, and infrequent optic nerve damage; posterior subcapsular cataract formation; and delayed wound healing.

Secondary Infection: The development of secondary infection has occurred after use of combinations containing steroids and antimicrobials. Fungal infections of the cornea are particularly prone to develop coincidentally with long-term applications of steroids. The possibility of fungal invasion must be considered in any persistent corneal ulceration where steroid treatment has been used.

Secondary bacterial ocular infection following suppression of host responses also occurs.

DOSAGE AND ADMINISTRATION:

Apply a small amount into the conjunctival sac(s) up to three or four times daily, or may be used adjunctively with Neomycin and Polymyxin B Sulfates and Dexamethasone Ophthalmic Suspension at bedtime.

How to apply Neomycin and Polymyxin B Sulfates and Dexamethasone Ophthalmic Ointment:

1. Tilt your head back.

2. Place a finger on your cheek just under your eye and gently pull down until a "V" pocket is formed between your eyeball and your lower lid.

3. Place a small amount (about 1/2 inch) of Neomycin and Polymyxin B Sulfates and Dexamethasone Ophthalmic Ointment in the "V" pocket. Do not let the tip of the tube touch your eye.

4. Look downward before closing your eye.

Not more than 8 grams should be prescribed initially and the prescription should not be refilled without further evaluation as outlined in PRECAUTIONS above.

HOW SUPPLIED:

Neomycin and Polymyxin B Sulfates and Dexamethasone Ophthalmic Ointment USP is supplied in an ophthalmic tube in the following size:

3.5 gram tube – NDC 63187-669-35

Storage:

Store between 15°-25° C (59°-77° F).

KEEP OUT OF REACH OF CHILDREN.

DO NOT USE IF CAP AND NECKRING ARE NOT INTACT.

FOR OPHTHALMIC USE ONLY.

Revised November 2007

Bausch & Lomb Incorporated
Tampa, FL 33637
©Bausch & Lomb Incorporated

Relabeled by:

Proficient Rx LP
Thousand Oaks, CA 91320

9114002 (Folded)
9114102 (Flat)

Principal Display Panel

NDC 63187-669-35

Neomycin and Polymyxin B Sulfates and Dexamethasone Ophthalmic Ointment USP

(Sterile)

Rx only

[icon- eye] [icon- ointment] [icon- 3.5gm]

Net wt. 1/8 oz
(3.5g)